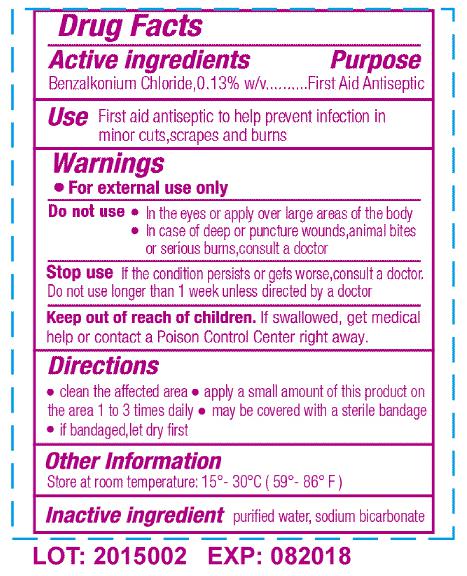 DRUG LABEL: BZK Antiseptic Swab
NDC: 80514-003 | Form: SWAB
Manufacturer: JIANGSU HAIDA INTERNATIONAL TRADING CO., LTD.
Category: otc | Type: HUMAN OTC DRUG LABEL
Date: 20231226

ACTIVE INGREDIENTS: BENZALKONIUM CHLORIDE 0.13 g/100 g
INACTIVE INGREDIENTS: WATER; SODIUM BICARBONATE

ACTIVE INGREDIENTS

Benzalkonium Chloride 0.13%

Purpose

First Aid Antiseptic.

USE

First aid antiseptic to help prevent infection in minor cuts,scrapes and burns.

WARNINGS

For external use only.

Do not use

In the eyes or apply over large areas of the body.

In case of deep or puncture wounds,animal bites or serious burns,consult a doctor.

Stop use

If the condition persists or gets worse,consult a doctor.

Do not use longer than 1 week unless directed by a doctor.

DIRECTIONS

Clean the affected area.

Apply a small amount of this product on the area 1 to 3 times daily.

May be covered with a sterile bandage.

If bandaged,let dry first.

Other Information

Store at room temperature:15-30℃(59-86℉)

INACTIVE INGREDIENT

Purified water, sodium bicarbonate.

Keep out of reach of children. if swallowed get medical help or contact Poison control Center right away.

DOSAGE AND ADMINISTRATION

Apply a small amount of this product on the area 1 to 3 times daily.